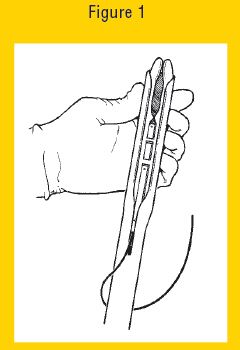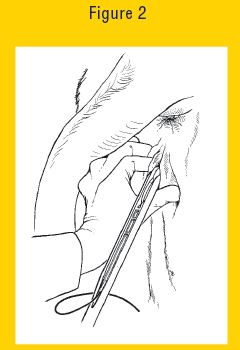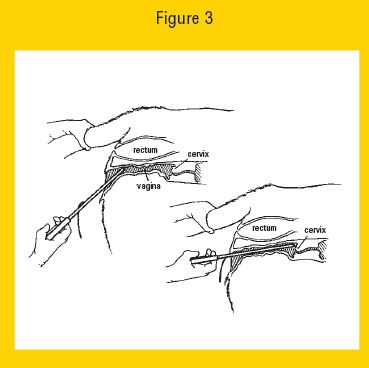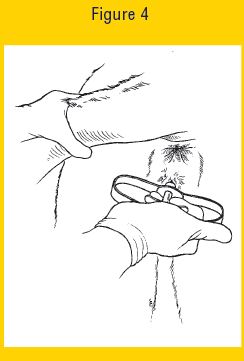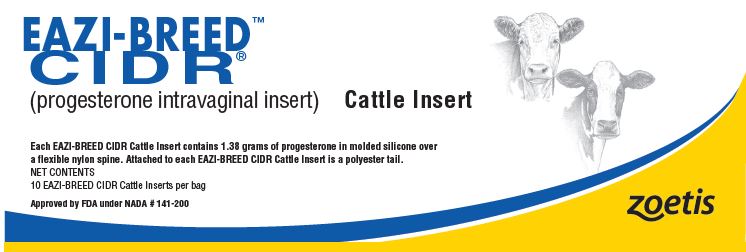 DRUG LABEL: EAZI-BREED CIDR Cattle
NDC: 54771-5207 | Form: INSERT, EXTENDED RELEASE
Manufacturer: Zoetis Inc.
Category: animal | Type: OTC ANIMAL DRUG LABEL
Date: 20220614

ACTIVE INGREDIENTS: PROGESTERONE 1.38 g/1 1

EAZI-BREED™
CIDR®

EAZI-BREED™

CIDR®

(progesterone intravaginal insert)

Cattle Insert

Each EAZI-BREED CIDR Cattle Insert contains 1.38 grams of progesterone in molded silicone over a flexible nylon spine. Attached to each EAZI-BREED CIDR Cattle Insert is a polyester tail.
NET CONTENTS
10 EAZI-BREED CIDR Cattle Inserts per bag
Approved by FDA under NADA # 141-200

DRUG FACTS

Active Ingredient: Progesterone, 1.38 grams per EAZI-BREED CIDR Cattle Insert

Uses

• Synchronization of estrus in lactating dairy cows, suckled beef cows, and replacement beef and dairy heifers
• Induction of estrous cycles in anestrous lactating dairy cows
• Synchronization of the return to estrus in lactating dairy cows inseminated at the immediately preceding estrus
• Advancement of first postpartum estrus in suckled beef cows
• Advancement of first pubertal estrus in replacement beef heifers
Removal of the EAZI-BREED CIDR Cattle Insert on treatment Day 7 results in a rapid fall in plasma progesterone levels, which results in the occurrence of estrus in those animals responding to treatment.

WARNINGS

Withdrawal Periods: Neither a pre-slaughter withdrawal interval nor a milk discard time is required when this product is used according to label directions.
User Safety Warning: Avoid contact with skin by wearing protective gloves when handling the inserts. Not for use in humans. Keep out of reach of children.
Environmental Warning: Store used (removed) EAZI-BREED CIDR Cattle Inserts in a plastic bag or other sealable container until they can be properly disposed in accordance with applicable local, state and Federal regulations.

DO NOT USE

• An insert more than once. To prevent the potential transmission of venereal and blood born disease the EAZI-BREED CIDR Cattle Insert should be disposed after a single use.
• In beef or dairy heifers of insufficient size or age for breeding or in cattle with abnormal, immature or infected genital tracts.
• In beef cows that are less than 20 days postpartum for synchronization of estrus or advancement of first postpartum estrus because safety and effectiveness have not been evaluated.
• In lactating dairy cows less than 40 days postpartum for synchronization of estrus or synchronization of the return to estrus because safety and effectiveness have not been evaluated.
• In anestrous lactating dairy cows less than 42 days or greater than 78 days postpartum for induction of estrous cycles because safety and effectiveness have not been evaluated

YOU MAY NOTICE

• Increased loss of EAZI-BREED CIDR Cattle Inserts in animals housed under crowded conditions, especially in heifers. Avoid crowded conditions during treatment as other cattle, particularly heifers, may remove EAZI-BREED CIDR Cattle Inserts by pulling on the tail of the EAZI-BREED CIDR Cattle Insert. If loss rates are high re-evaluate insertion technique and cattle handling facilities.
• Clear, cloudy, yellow or bloody mucus on the outside of EAZI-BREED CIDR Cattle Insert when removed from animals. The mucus may have an offensive odor. This is a result of irritation to the vaginal lining by the presence of the EAZI-BREED CIDR Cattle Insert, and generally clears between the time of removal and insemination. Such irritation does not affect fertility at inseminations following treatment.
• Use of EAZI-BREED Cattle Insert for periods of longer than 7 days may result in reduced fertility.
• Reduced conception rates to inseminations conducted immediately following removal of the EAZI-BREED CIDR Cattle Insert when used for induction of estrous cycles in anestrous lactating dairy cows. Such reductions in conception rate are not expected to result in reduced pregnancy rates.
• Reduced pregnancy rates to inseminations conducted immediately prior to administration of EAZI-BREED CIDR Cattle Inserts used for synchronizing the return to estrus in lactating

DIRECTIONS

Lactating Dairy Cows
For Synchronization of Estrus in Lactating Dairy Cows:
• Administer one EAZI-BREED CIDR Cattle Insert per animal and remove 7 days later (for example if administered on a Monday remove the following Monday).
• Administer 5 mL LUTALYSE® Sterile Solution at the time of removal of the EAZI-BREED CIDR Cattle Insert.
• Observe animals for signs of estrus on Days 2 to 5 after removal of the EAZI-BREED CIDR Cattle Insert and inseminate animals found in estrus following typical herd practices.

For Induction of Estrous Cycles in Anestrous Lactating Dairy Cows:
• For induction of estrous cycles in anestrous lactating dairy cows, anestrous dairy cows can be identified using any of the following methods:
- Cows not observed in estrus since calving.
- Cows diagnosed twice without a corpus luteum on either ovary via ultrasonography at a 7 to 14 day interval, such as on Day 35 and Day 42 post calving.
- Cows with low concentration of progesterone in two blood or milk samples collected at a 7 to 14 day interval, such as samples collected on Day 35 and 42 post calving.
• Administer one EAZI-BREED CIDR Cattle Insert per anestrous cow and remove 7 days later (for example if administered on a Monday remove the following Monday).
• If insemination is intended, observe cows on Days 2 to 5 after removal of the EAZI-BREED CIDR Cattle Insert and inseminate animals found in estrus following typical herd practices.

For Synchronization of the Return to Estrus in Lactating Dairy Cows Inseminated at the Immediately Preceding Estrus:
• Administer one EAZI-BREED CIDR Cattle Insert per animal 14±1 days after insemination. Remove EAZI-BREED CIDR Cattle Insert 7 days later (for example, if administered on a Monday
remove on the following Monday).
• Observe animals for signs of estrus on Days 1 to 3 after removal of the EAZI-BREED CIDR Cattle Insert and inseminate animals about 12 hours after onset of estrus.
• Note: Do not administer LUTALYSE® Sterile Solution or other prostaglandin products to cows for synchronization of the return to estrus, as this will interrupt pregnancy that may have occurred at the immediately previous insemination.

Suckled Beef Cows, Replacement Beef and Dairy Heifers: For synchronization of estrus in suckled beef cows and replacement beef and dairy heifers, advancement of first postpartum estrus in suckled beef cows, and advancement of first pubertal estrus in beef heifers:
• Administer one EAZI-BREED CIDR Cattle Insert per animal for 7 days (for example, if administered on a Monday remove on the following Monday).
• Inject 5 mL LUTALYSE® Sterile Solution (equivalent to 5 mg/mL dinoprost) 1 day prior to EAZI-BREED CIDR Cattle Insert removal, on Day 6 of the 7 day administration period.
• Observe animals for signs of estrus on Days 1 to 3 after removal of the EAZI-BREED CIDR Cattle Insert and inseminate animals about 12 hours after onset of estrus.

Insertion:
1. Avoid contact with skin by wearing protective gloves when handling inserts.
2. Only use the specially designed EAZI-BREED CIDR Cattle Insert Applicator for administration.
3. Restrain cattle appropriately (head catch, squeeze chute, gate, etc.) prior to administration.
4. Wash the EAZI-BREED CIDR Cattle Insert Applicator in a non-irritating antiseptic solution, and then lubricate the front portion of the EAZI-BREED CIDR Cattle Insert Applicator with a veterinary obstetrical lubricant.
5. Push the flexible tail end of the EAZI-BREED CIDR Cattle Insert into the EAZI-BREED CIDR Cattle Insert Applicator taking care to assure the tail is extending upward through the slot of the EAZI-BREED CIDR Cattle Insert Applicator and is pointed toward the handle.
6. Fold the wings of the EAZI-BREED CIDR Cattle Insert to make it longer and continue to advance the EAZI-BREED CIDR Cattle Insert into the applicator until it is fully seated. When fully seated only the tips of the wings should protrude (one half inch) from the end of the EAZI-BREED CIDR Cattle Insert Applicator (see Figure 1 below).
7. Lubricate the protruding tips of the wings of the EAZI-BREED CIDR Cattle Insert with veterinary obstetrical lubricant.
8. Lift the tail of the animal and clean the exterior of the vulva.
9. Open the lips of the vulva and gently place the loaded EAZI-BREED CIDR Cattle Insert Applicator through the vulva. The slot in the EAZI-BREED CIDR Cattle Insert Applicator should face upwards (see Figure 2 below).
10. Once the loaded EAZI-BREED CIDR Cattle Insert Applicator is past the vulva slope the EAZI-BREED CIDR Cattle Insert Applicator slightly upwards (35-45° angle) by lowering the handle, and then forward, without forcing, until the EAZI-BREED CIDR Cattle Insert Applicator is fully inserted or resistance is felt (see Figure 3 below).
11. Squeeze the finger grips within the handle of the EAZI-BREED CIDR Cattle Insert Applicator to deposit the EAZI-BREED CIDR Cattle Insert in the anterior vagina (see Figure 4 below) and then pull the EAZI-BREED CIDR Cattle Insert Applicator backwards to remove it from the vagina.
12. With the EAZI-BREED CIDR Cattle Insert correctly placed, with the wings open in the anterior portion of the vagina, the tail of the EAZI-BREED CIDR Cattle Insert should be visible, pointing downward from the vulva of the animal. Tails of EAZI-BREED CIDR Cattle Inserts that protrude more than 2.5 inches from the vulva may be clipped to minimize removal by other animals.

Removal:
1. Remove EAZI-BREED CIDR Cattle Inserts by pulling, gently but firmly, on the protruding polyester tail.
2. EAZI-BREED CIDR Cattle Inserts have been reported to reverse direction within the vagina; therefore, if the polyester tail of the insert is not visible on the day of removal, check the vagina to determine if an insert is present.
3. Used (removed) EAZI-BREED CIDR Cattle Inserts still contain some progesterone. Used EAZI-BREED CIDR Cattle Inserts must be stored in a sealable container until disposed. Sealed bag/container with used EAZI-BREED CIDR Cattle Inserts must be properly disposed in accordance with applicable local, state and Federal regulations.

Figure 1 Eazi-Breed CIDR

Figure 2 Eazi Breed CIDR

Figure 3 Eazi Breed CIDR

Figure 4 Eazi Breed CIDR

OTHER INFORMATION

Store at controlled room temperature 20° to 25°C (68° to 77°F) with excursions between 15° to 30°C (59° to 86°F).

To report suspected adverse events, for technical assistance or to obtain a copy of the SDS, contact Zoetis at 1-888-963-8471. For additional information about adverse drug experience reporting for animal drugs, contact FDA at 1-888 -FDA-VETS or http://www.fda.gov/reportanimalae.
Restricted Drug (California) - use only as directed
Distributed by: Zoetis Inc.
Kalamazoo, MI 49007
39006604-04/19

Inactive Ingredients

Inactive Ingredients: silicone rubber, nylon and polyester.
EAZI-BREED is a trademark and CIDR is a registered trademark of DEC International, NZ, Ltd.